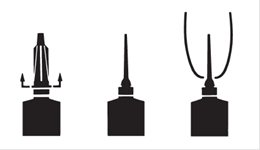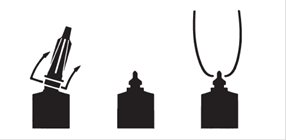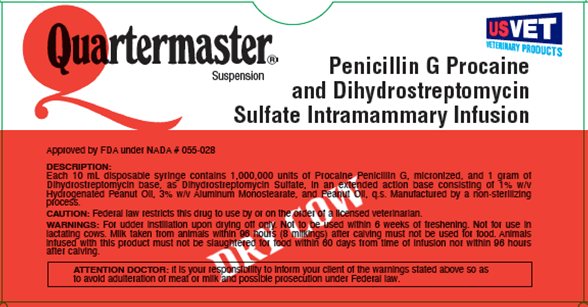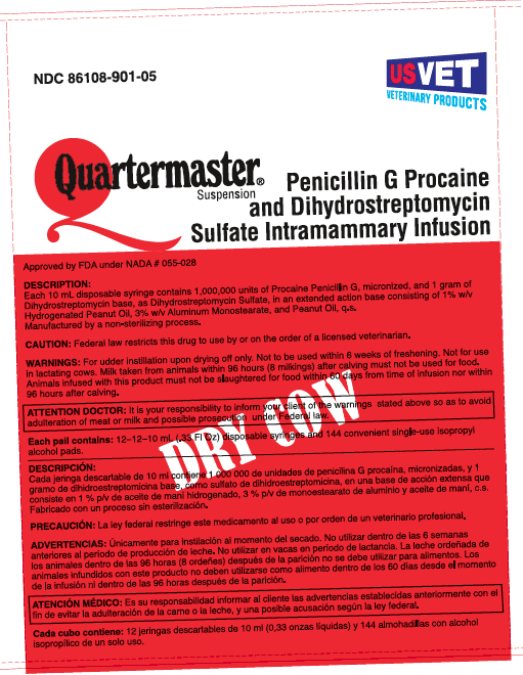 DRUG LABEL: Quartermaster
NDC: 86108-901 | Form: SUSPENSION
Manufacturer: US Vet Inc
Category: animal | Type: PRESCRIPTION ANIMAL DRUG LABEL
Date: 20251104

ACTIVE INGREDIENTS: PENICILLIN G PROCAINE 1000000 [iU]/10 mL; DIHYDROSTREPTOMYCIN SULFATE 1 g/10 mL
INACTIVE INGREDIENTS: ALUMINUM MONOSTEARATE; PEANUT OIL; HYDROGENATED PEANUT OIL

Quartermaster Suspension (Penicillin g procaine and dihydrostreptomycin sulfate intramammary infusion)

ATTENTION DOCTOR:

It is your responsibility to inform your client of the warnings stated above so as to avoid adulteration of meat or milk and possible prosecution under Federal law.

ATENCIÓN MÉDICO:

Es su responsabilidad informar al cliente las advertencias establecidas anteriormente con el fin de evitar la adulteración de la carne o la leche, y una posible acusación según la ley federal.

DESCRIPTION

Each 10 mL disposable syringe contains 1,000,000 units of Procaine Penicillin G, micronized, and 1 gram of Dihydrostreptomycin base, as Dihydrostreptomycin Sulfate, in an extended action base consisting of 1% w/v Hydrogenated Peanut Oil, 3% w/v Aluminum Monostearate, and Peanut Oil, q.s. Manufactured by a non-sterilizing process.

DESCRIPCIÓN:

Cada jeringa descartable de 10 ml contiene 1 000 000 de unidades de penicilina G procaína, micronizadas, y 1 gramo de dihidroestreptomicina base, como sulfato de dihidroestreptomicina, en una base de acción extensa que consiste en 1 % p/v de aceite de maní hidrogenado, 3 % p/v de monoestearato de aluminio y aceite de maní, c.s. Fabricado con un proceso sin esterilización.

ACTION

Infusion of antibiotics at the start of the drying off period has the following advantages: (1) it is active against existing infections; (2) it is prophylactic against new infections, during the time when cattle are likely to become infected [1]; (3) the antibiotic remains in the udder for a sufficiently long period to accomplish the intended objective and is not diluted with milk, as is the case in lactation therapy; (4) the danger of drug residues in the milk is reduced.

Antibiotic control is to be considered an adjunct to good herd hygiene management and milking management. Detailed field studies in England and the United States have demonstrated that a program consisting of treatment, at the time of drying off, with a highly effective antibiotic preparation in a slow-release base, and routine dipping of teats after each milking with an effective disinfectant, markedly reduces the incidence of all udder infections at calving [2,3,4].

It has recently been recommended that a disinfectant teat dip be used on unmilked cows, or at least be used for 10 days before parturition [5], to reduce the bacterial challenge to the depleted levels of antibiotic in the teat as freshening is approached [6].

When the herd infection level has been reduced, or when herds are not heavily infected initially, it may be desirable to be selective in treating dry quarters [7].

ACCIÓN:

La infusión de antibióticos al comienzo del período de secado tiene las siguientes ventajas: (1) es activa contra las infecciones existentes; (2) es profiláctica contra las nuevas infecciones durante el período en el que el ganado es propenso a contraer infecciones [1]; (3) el antibiótico permanence en la ubre por un período lo suficientemente largo como para lograr el objetivo y no se diluye con la leche, como pasa con la terapia en período de lactancia; (4) se reduce el peligro de que queden residuos del medicamento en la leche.

El control con antibióticos debe considerarse un auxiliar de la buena gestión de higiene del Ganado y la gestión del ordeñe. Estudios de campo detallados realizados en Inglaterra y Estados Unidos han demostrado que un programa constituido por un tratamiento al momento del secado, con una preparación de antibióticos de liberación lenta altamente efectiva, y el sellado frecuente de los pezones con un desinfectante eficaz después de cada ordeñe, reducen considerablemente la incidencia de todas las infecciones de ubre en la parición [2, 3, 4].

Recientemente, se ha recomendado usar un sellador desinfectante de pezones en vacas no ordeñadas, o al menos usarlo 10 días antes del parto [5] para reducir el riesgo bacteriano a los niveles más bajos de antibiótico en el pezón cuando se acerca el período de producción de leche [6].

Cuando se haya reducido el nivel de infección del ganado, o en caso de que el ganado no esté muy infectado, es conveniente ser selectivo en el tratamiento de cuartos secos [7].

INDICATIONS

For intramammary use to reduce the frequency of existing infection and to prevent new infections with Staphylococcus aureus in dry cows.

INDICACIONES:

Uso intramamario para reducir la frecuencia de la infección existente y prevenir nuevas infecciones por Staphylococcus aureus en vacas secas.

DIRECTIONS FOR USING THE FLEXIBLE TIP SYSTEM:

The flexible tip is designed to provide the choice of either insertion of the full cannula, as has traditionally been practiced, or insertion of no more than 1/8 inch of the cannula, as recommended by the National Mastitis Council.

a. Full Insertion: Remove the white end cap by pulling straight up as shown. Gently insert the full cannula into the teat canal; carefully infuse the product.

a.

b. Partial

Insertion: Remove both the white end cap and the red cannula by pushing sideways as shown. Gently insert the exposed white tip into the teat canal; carefully infuse the product.

b.

INSTRUCCIONES DE USO DEL SISTEMA DE PUNTA FLEXIBLE:

La punta flexible está diseñada para brindar la opción de una inserción completa de la cánula, como se ha realizado tradicionalmente, o la inserción de no más de 1/8 pulgada de la cánula, como lo recomienda el Concejo Nacional de Mastitis.

a. Inserción completa: Tire hacia arriba para qui tar el tapón blanco, como se muest ra. Inserte suavemente toda la cánula en el canal del pezón; infunda el producto con cuidado.

a.

b. Inserción parcial: Retire el tapón blanco y la cánula roja tirando de los laterales, como se muestra. Inserte suavemente la punta blanca expuesta en el canal del pezón; infunda el product con cuidado.

b.

DIRECTIONS FOR USE:

At the last milking prior to drying off, completely milk out cow. Warm the syringe containing Quartermaster Suspension to body temperature; choose the desired insertion length (full or partial) and insert tip into teat canal; slowly infuse the entire contents. Instill the contents of one syringe into each quarter. Discard the syringe after use. Treated teats should then be dipped into an effective teat dip. The teat or quarter should not be manipulated again until the cow freshens. To achieve and maintain a lower frequency of infection, proper dipping of teats during lactation is recommended.

Shake vigorously for 10 seconds immediately before using.

INSTRUCCIONES DE USO:

En el último ordeñe, antes del secado, ordeñe la vaca por completo. Entibie la jeringa que contiene la Suspensión Quartermaster a temperatura corporal; elija el largo de inserción deseado (completa o parcial) e inserte la punta en el canal del pezón; infunda lentamente todo el contenido. Instile el contenido de una jeringa en cada cuarto. Deseche la jeringa después de usarla. Los pezones tratados deben sumergirse en un sellador de pezones eficaz. No se deben volver a manipular el pezón ni el cuarto hasta que la vaca para. Para lograr reducer la frecuencia de infección, se recomienda el sellado adecuado de los pezones durante la lactancia.

Agitar con fuerza por 10 segundos justo antes de usar.

WARNINGS

For udder instillation upon drying off only. Not to be used within six (6) weeks of freshening. Not for use in lactating cows. Milk taken from animals within 96 hours (8 milkings) after calving must not be used for food. Animals infused with this product must not be slaughtered for food within 60 days from time of infusion nor within 96 hours after calving.

ADVERTENCIAS:

Únicamente para inst i lación al momento del secado. No utilizar dentro de las seis (6) semanas del período de producción de leche. No utilizar en vacas en período de lactancia. La leche ordeñada de los animales dentro de las 96 horas (8 ordeñes) después de la parición no se debe utilizar para alimentos. Los animales infundidos con este product no deben utilizarse como alimento dentro de los 60 días desde el momento de la infusión ni dentro de las 96 horas después de la parición.

CAUTION:

Federal law restricts this drug to use by or on the order of a licensed veterinarian.

PRECAUCIÓN:

La ley federal restringe este medicamento al uso o por orden de un veterinario profesional.

STORAGE CONDITIONS:

Store at controlled room temperature 20° to 25°C (68° to 77°F). Store under dry conditions.

CONDICIONES DE ALMACENAMIENTO:

Almacenar en una habitación con temperature controlada de 20 ºC a 25 ºC (68 ºF a 77 ºF). Almacenar en un lugar seco.

HOW SUPPLIED

Quartermaster Suspension is supplied as:

Packers of 12–10 mL (.33 Fl Oz) disposable syringes with 12 convenient single-use isopropyl alcohol pads NDC 86108-901-03

Pails of 144–10 mL (.33 Fl Oz) disposable syringes with 144 convenient single-use isopropyl alcohol pads NDC 86108-901-05

PRESENTACIÓN:

La suspensión Quartermaster se presenta de la siguiente forma:

Paquetes de 12–jeringas descartables de 10 ml (0,33 onzas líquidas) con 12 almohadillas con alcohol isopropílico de un solo uso . . . . . . . . . . . . . . . . . . . . . . NDC 86108-901-03

Cubos de 144–jeringas descartables de 10 ml (0,33 onzas líquidas) con 144 almohadillas con alcohol isopropílico de un solo uso . . . . . . . . . . . . . . . . . . . . . NDC 86108-901-05

REFERENCES:

[1] Smith, A.; Westgarth, D.R.; Jones, M.R.; Neave, F.K.; Dodd, F.H.; & Brander, G.C., Methods of Reducing the Incidence of Udder Infection in Dry Cows, VETERINARY RECORD 81:504-510, 1967.

[2] Dodd, F.H. & Neave, F.K., Mastitis Control, N.I.R.D. BIENNIAL REVIEWS 1970, pp. 21-60.

[3] Roberts, S.J.; Meek, A.M.; Natzke, R.; & Guthrie, R., A Mastitis Control Program Combining Teat Dipping & Dry Cow Therapy, XIX WORLD VETERINARY CONGRESS (Mexico City, 8/15-21/71), PROCEEDINGS 3:935-939, 1971.

[4] Newbould, F.H.S.; Carey, P.G.; & Barnum, D.A., The Numbers of Intramammary Infections & Teat Duct Colonizations in a Herd of Twins During a Hygiene Experiment, CANADIANJOURNAL OF COMPARATIVE MEDICINE 34:203-208, 1970.

[5] Neave, F.K. & Jackson, E.R., The Prevention of Intramammary Infection, pp. 15-24 in The Control of Bovine Mastitis (Proceedings, Joint Meeting, British Cattle Veterinary Association & The Agricultural Development Association, Reading University. 1/5-6/71), N.I.R.D., 1971.

[6] Feagan, J.T.; Hehir, A.F.; & White, B.R., The Effectiveness in Control of Mastitis of Iodine as a Post Milking Teat Dip, AUSTRALIAN JOURNALOF DAIRY TECHNOLOGY 25: 87-90, 1970.

[7] Supplement to Current Concepts of Bovine Mastitis. The National Mastitis Council Inc.,Washington, D.C. 22003, 1972, page 7.

BIBLIOGRAFÍA:

[1] Smith, A.; Westgarth, D.R.; Jones, M.R.; Neave, F.K.; Dodd, F.H.; & Brander, G.C., Methods of Reducing the Incidence of Udder Infection in Dry Cows, VETERINARY RECORD 81:504-510, 1967.

[2] Dodd, F.H. & Neave, F.K., Mastitis Control, N.I.R.D. BIENNIAL REVIEWS 1970, pp. 21-60.

[3] Roberts, S.J.; Meek, A.M.; Natzke, R.; & Guthrie, R., A Mastitis Control Program Combining Teat Dipping & Dry Cow Therapy, XIX WORLD VETERINARY CONGRESS (Mexico City, 8/15-21/71), PROCEEDINGS 3:935-939, 1971.

[4] Newbould, F.H.S.; Carey, P.G.; & Barnum, D.A., The Numbers of Intramammary Infections & Teat Duct Colonizations in a Herd of Twins During a Hygiene Experiment, CANADIANJOURNAL OF COMPARATIVE MEDICINE 34:203-208, 1970.

[5] Neave, F.K. & Jackson, E.R., The Prevention of Intramammary Infection, pp. 15-24 in The Control of Bovine Mastitis (Proceedings, Joint Meeting, British Cattle Veterinary Association & The Agricultural Development Association, Reading University. 1/5-6/71), N.I.R.D., 1971.

[6] Feagan, J.T.; Hehir, A.F.; & White, B.R., The Effectiveness in Control of Mastitis of Iodine as a Post Milking Teat Dip, AUSTRALIAN JOURNALOF DAIRY TECHNOLOGY 25: 87-90, 1970.

[7] Supplement to Current Concepts of Bovine Mastitis. The National Mastitis Council Inc.,Washington, D.C. 22003, 1972, page 7.

Manufactured for:

US VET Inc.

Liverpool, NY 13088

Quartermaster is a trademark of West Agro, Inc.

Quartermaster es una marca de West Agro, Inc.

Approved by FDA under NADA # 055-028

Rev. 06/2025

PACKAGE/LABEL PRINCIPAL DISPLAY PANEL

NDC 86108-901-03

Quartermaster Suspension

Penicillin G Procaine and Dihydrostreptomycin Sulfate Intramammary Infusion

US VET Inc.

PACKAGE/LABEL PRINCIPAL DISPLAY PANEL

NDC 86108-901-05

Quartermaster Suspension

Penicillin G Procaine and Dihydrostreptomycin Sulfate Intramammary Infusion

US VET Inc.